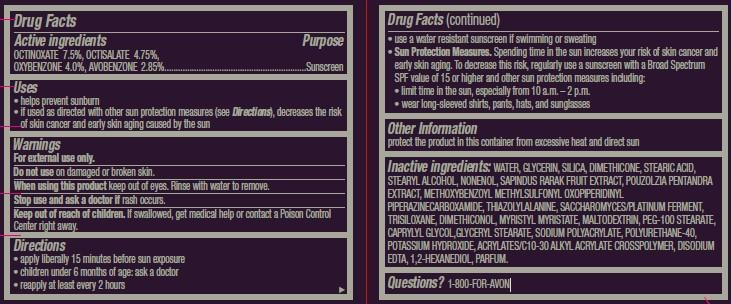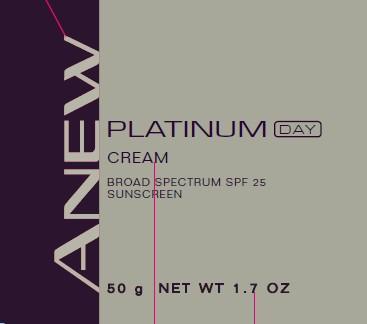 DRUG LABEL: ANEW
NDC: 10096-0224 | Form: CREAM
Manufacturer: New Avon LLC
Category: otc | Type: HUMAN OTC DRUG LABEL
Date: 20190101

ACTIVE INGREDIENTS: OCTINOXATE 75 mg/1 g; OCTISALATE 47.5 mg/1 g; OXYBENZONE 40 mg/1 g; AVOBENZONE 28.5 mg/1 g
INACTIVE INGREDIENTS: WATER

Anew Platinum Day Cream

Active ingredients
OCTINOXATE 7.5%, OCTISALATE 4.75%,
OXYBENZONE 4.0%, AVOBENZONE 2.85%..................................

Purpose
............................Sunscreen

Uses
• helps prevent sunburn
• if used as directed with other sun protection measures (see Directions), decreases the risk of skin cancer and early skin aging caused by the sun

Warnings
For external use only.

Do not use on damaged or broken skin.

When using this product keep out of eyes. Rinse with water to remove.

Stop use and ask a doctor if rash occurs.

Keep out of reach of children. If swallowed, get medical help or contact a Poison Control Center right away.

Directions
• apply liberally 15 minutes before sun exposure
• children under 6 months of age: ask a doctor
• reapply at least every 2 hours
• use a water resistant sunscreen if swimming or sweating
• Sun Protection Measures. Spending time in the sun increases your risk of skin cancer and early skin aging. To decrease this risk, regularly use a sunscreen with a Broad Spectrum SPF value of 15 or higher and other sun protection measures including:
• limit time in the sun, especially from 10 a.m. – 2 p.m.
• wear long-sleeved shirts, pants, hats, and sunglasses

Other Information
protect the product in this container from excessive heat and direct sun

INACTIVE INGREDIENT

Inactive ingredients: WATER, GLYCERIN, SILICA, DIMETHICONE, STEARIC ACID, STEARYL ALCOHOL, NONENOL, SAPINDUS RARAK FRUIT EXTRACT, POUZOLZIA PENTANDRA EXTRACT, METHOXYBENZOYL METHYLSULFONYL OXOPIPERIDINYL PIPERAZINECARBOXAMIDE, THIAZOLYLALANINE, SACCHAROMYCES/PLATINUM FERMENT, TRISILOXANE, DIMETHICONOL, MYRISTYL MYRISTATE, MALTODEXTRIN, PEG-100 STEARATE, CAPRYLYL GLYCOL,GLYCERYL STEARATE, SODIUM POLYACRYLATE, POLYURETHANE-40, POTASSIUM HYDROXIDE, ACRYLATES/C10-30 ALKYL ACRYLATE CROSSPOLYMER, DISODIUM EDTA, 1,2-HEXANEDIOL, PARFUM.

Questions? 1-800-FOR-AVON